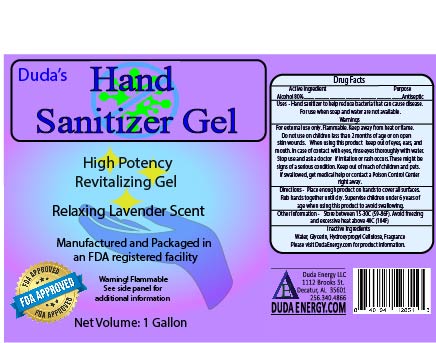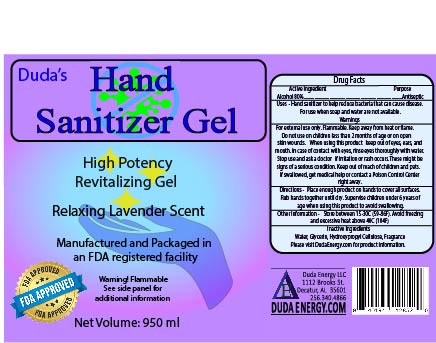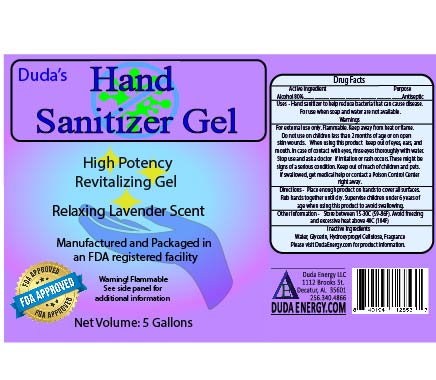 DRUG LABEL: Dudas Hand Sanitizer Gel
NDC: 77209-9664 | Form: GEL
Manufacturer: Duda Energy LLC
Category: otc | Type: HUMAN OTC DRUG LABEL
Date: 20220127

ACTIVE INGREDIENTS: ALCOHOL 80 L/100 L
INACTIVE INGREDIENTS: GLYCERIN 2.5 L/100 L; HYDROXYPROPYL CELLULOSE, UNSPECIFIED 1.1 L/100 L; WATER; LAVENDER OIL

Inactive ingredients

=

DOSAGE AND ADMINISTRATION

- Place enough product on hands to cover all surfaces. Rub hands together until dry.
- Supervise children under 6 years of age when using this product to avoid swallowing.

STORAGE AND HANDLING

- store in a well-ventilated place and keep cool.